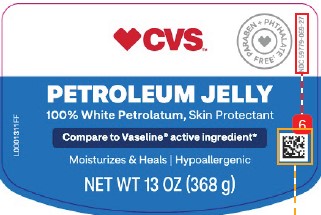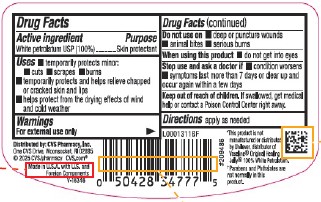 DRUG LABEL: Petroleum
NDC: 59779-069 | Form: JELLY
Manufacturer: CVS Pharmacy, Inc.
Category: otc | Type: HUMAN OTC DRUG LABEL
Date: 20260202

ACTIVE INGREDIENTS: PETROLATUM 1 g/1 g

CVS 069.001/069AA
Petroleum Jelly

Active ingredient

White petrolatum USP (100%)

Purpose

Skin Protectant

Uses

- temporarily protects minor: • cuts • scrapes • burns
- temporarily protects and helps relieve chapped or cracked skin and lips
- helps protect from the drying effects of wind and cold weather

Warnings

For external use only

Do not use on

- deep or puncture wounds
- animal bites
- serious burns

When using this product

- do not get into eyes

Stop use and ask a doctor if

- condition worsens
- symptoms last more than 7 days or clear up and occur again within a few days

Keep out of reach of children.

If swallowed, get medical help or contact a Poison Control Center right away.

Directions

apply as needed

Inactive Ingredient

None

ADVERSE REACTION

Distributed by: CVS Pharmacy, Inc.

One CVS Drive, Woonsocket, RI 02895

©2025 CVS/pharmacy CVS.com

Made in the U.S.A. with U.S. and foreign components.

Disclaimers

*This product is not manufactured or distributed by Unilever, distributor of Vaseline®Original Healing Jelly®100% White Petrolatum.

†Parabens and Phthalates are not normally in this product.

principal display panel

CVS™

PARABEN + PHTHALATE FREE†

NDC 59779-069-27

PETROLEUM JELLY

100%White Petrolatum, Skin Protectant

Compare to Vaseline®active ingredient*

Moisturizes & Heals

Hypoallergenic

NET WT 13 OZ (368 g)